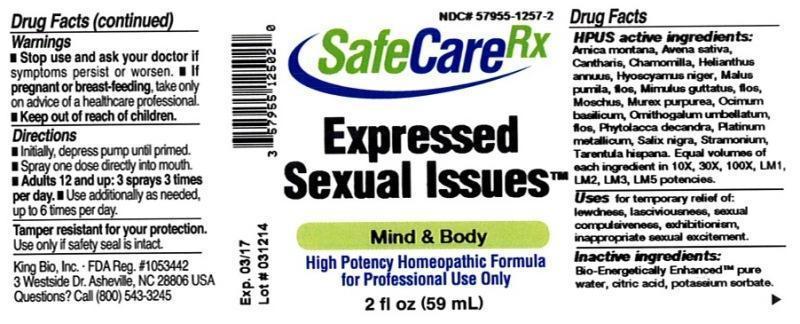 DRUG LABEL: Expressed Sexual Issues
NDC: 57955-1257 | Form: LIQUID
Manufacturer: King Bio Inc.
Category: homeopathic | Type: HUMAN OTC DRUG LABEL
Date: 20140417

ACTIVE INGREDIENTS: ARNICA MONTANA 10 [hp_X]/59 mL; AVENA SATIVA FLOWERING TOP 10 [hp_X]/59 mL; LYTTA VESICATORIA 10 [hp_X]/59 mL; MATRICARIA RECUTITA 10 [hp_X]/59 mL; HELIANTHUS ANNUUS FLOWERING TOP 10 [hp_X]/59 mL; HYOSCYAMUS NIGER 10 [hp_X]/59 mL; MALUS DOMESTICA FLOWER 10 [hp_X]/59 mL; MIMULUS GUTTATUS FLOWERING TOP 10 [hp_X]/59 mL; MOSCHUS MOSCHIFERUS MUSK SAC RESIN 10 [hp_X]/59 mL; HEXAPLEX TRUNCULUS HYPOBRANCHIAL GLAND JUICE 10 [hp_X]/59 mL; BASIL 10 [hp_X]/59 mL; ORNITHOGALUM UMBELLATUM FLOWERING TOP 10 [hp_X]/59 mL; PHYTOLACCA AMERICANA ROOT 10 [hp_X]/59 mL; PLATINUM 10 [hp_X]/59 mL; SALIX NIGRA BARK 10 [hp_X]/59 mL; DATURA STRAMONIUM 10 [hp_X]/59 mL; LYCOSA TARANTULA 10 [hp_X]/59 mL
INACTIVE INGREDIENTS: WATER; CITRIC ACID MONOHYDRATE; POTASSIUM SORBATE

Expressed Sexual Issues™

ACTIVE INGREDIENT

Drug Facts__________________________________________________________________________________________________________

HPUS active ingredients: Arnica montana, Avena sativa, Cantharis, Chamomilla, Helianthus annuus, Hyoscyamus niger, Malus pumila, flos, Mimulus guttatus, flos, Moschus, Murex purpurea, Ocimum basilicum, Ornithogalum umbellatum, flos, Phytolacca decandra, Platinum metallicum, Salix nigra, Stramonium, Tarentula hispana. Equal volumes of each ingredient in 10X, 30X, 100X, LM1, LM2, LM3, LM5 potencies.

INDICATIONS AND USAGE

Uses for temporary relief of: lewdness, lasciviousness, sexual compulsiveness, exhibitionism, inappropriate sexual excitement.

Inactive Ingredients:

Bio-Energetically Enhanced™ pure water, citric acid and potassium sorbate.

Warnings

- Stop use and ask your doctor if symptoms persist or worsen.
- If pregnant or breast-feeding, take only on advice of a healthcare professional.

- Keep out of reach of children.

Directions

- Initially, depress pump until primed.
- Spray one dose directly into mouth.
- Adults 12 and up: 3 sprays 3 times per day.
- Use additionally as needed, up to 6 times per day.

OTHER SAFETY INFORMATION

Tamper resistant for your protection. Use only if safety seal is intact.

PURPOSE

Uses for temporary relief of:

- lewdness
- lasciviousness
- sexual compulsiveness
- exhibitionism
- inappropriate sexual excitement